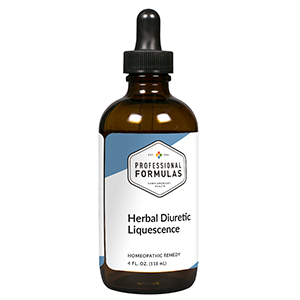 DRUG LABEL: Herbal Diuretic Liquescence
NDC: 63083-3011 | Form: LIQUID
Manufacturer: Professional Complementary Health Formulas
Category: homeopathic | Type: HUMAN OTC DRUG LABEL
Date: 20190815

ACTIVE INGREDIENTS: VALERIAN 2 [hp_X]/118 mL; ANHYDROUS CITRIC ACID 3 [hp_X]/118 mL; ANTIMONY CATION (3+) 3 [hp_X]/118 mL; GARLIC 6 [hp_X]/118 mL; SODIUM CHLORIDE 6 [hp_X]/118 mL; RAUWOLFIA SERPENTINA 6 [hp_X]/118 mL; RENIN 6 [hp_X]/118 mL; BOS TAURUS ARTERY 6 [hp_X]/118 mL; BEEF KIDNEY 6 [hp_X]/118 mL; MIDORIAMIN 6 [hp_X]/118 mL
INACTIVE INGREDIENTS: ALCOHOL; WATER

T11

ACTIVE INGREDIENTS

Valeriana officinalis 2X
Citricum acidum 3X
Potassium bitartrate 3X
Allium sativum 6X
Natrum muriaticum 6X
Rauwolfia serpentina 6X
Renin 6X
Collective arterial tissue 6X, 12X, 30X
Kidney 6X, 12X, 30X
Midbrain 6X, 12X, 30X

QUESTIONS

Professional Formulas

PO Box 2034 Lake Oswego, OR 97035

INDICATIONS

For the temporary relief of bloating, swelling of extremities, minor joint stiffness, weight gain, fatigue, or occasional headache.*

PURPOSE

*Claims based on traditional homeopathic practice, not accepted medical evidence. Not FDA evaluated.

WARNINGS

Consult a doctor if condition worsens or if symptoms persist. Keep out of the reach of children. In case of overdose, get medical help or contact a poison control center right away. If pregnant or breastfeeding, ask a healthcare professional before use.

Keep out of the reach of children.

PREGNANCY OR BREAST FEEDING

If pregnant or breastfeeding, ask a healthcare professional before use.

DIRECTIONS

Place drops under tongue 30 minutes before/after meals. Adults and children 12 years and over: Take one full dropper up to 2 times per day. Consult a physician for use in children under 12 years of age.

OTHER INFORMATION

Tamper resistant. If seal is broken, do not use. After opening, close container tightly and store at room temperature away from heat.

INACTIVE INGREDIENTS

20% ethanol, purified water.

LABEL

Est 1985

Professional Formulas

Complementary Health

Herbal Diuretic Liquescence

Homeopathic Remedy

4 FL. OZ. (118 mL)